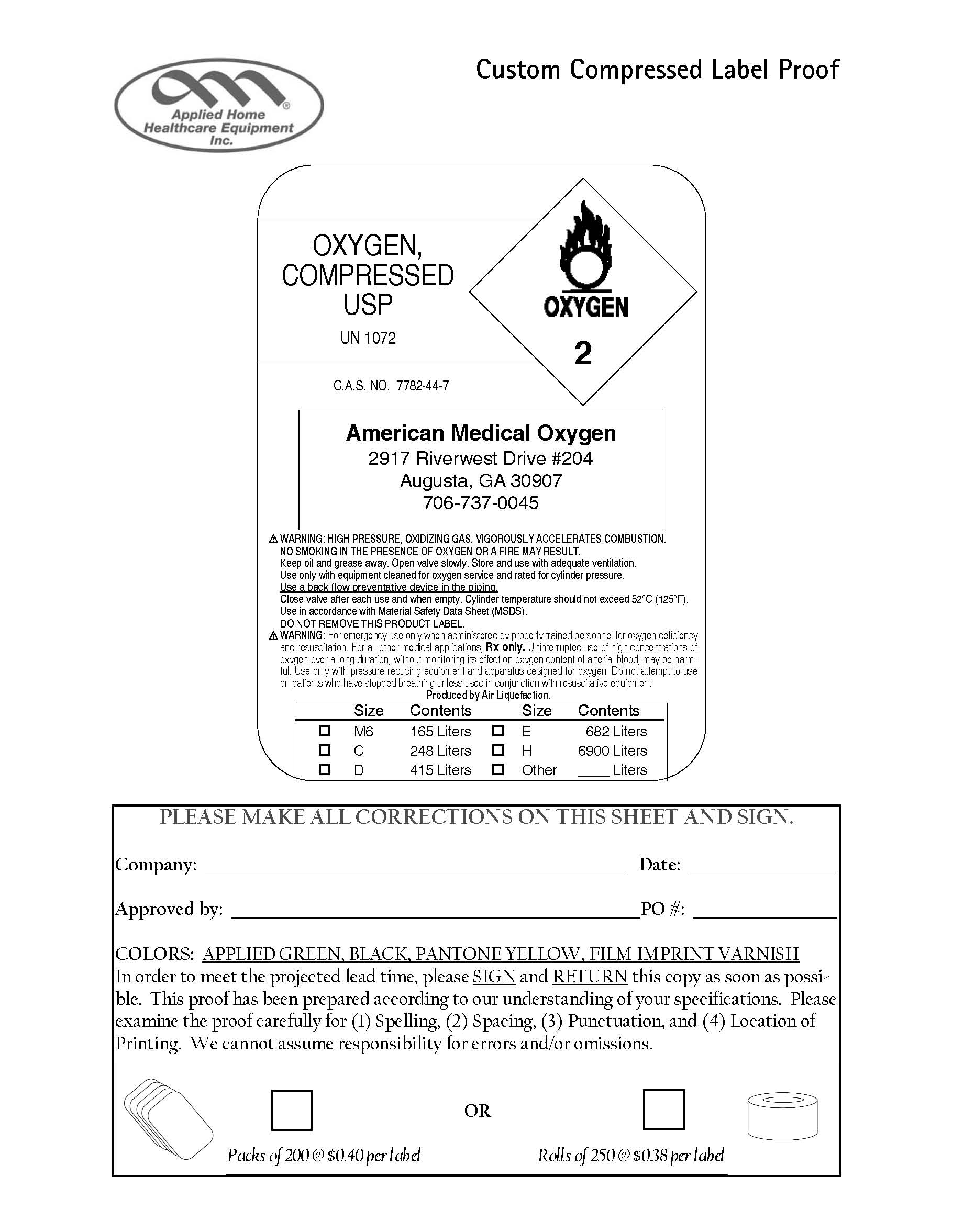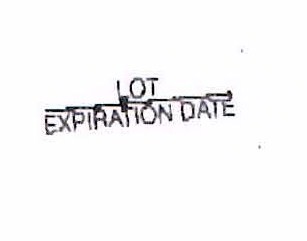 DRUG LABEL: Oxygen
NDC: 10453-0123 | Form: GAS
Manufacturer: Sunrise Medical Supply, Inc. dba American Medical Oxygen 
Category: prescription | Type: HUMAN PRESCRIPTION DRUG LABEL
Date: 20100113

ACTIVE INGREDIENTS: Oxygen 99 L/100 L

Oxygen